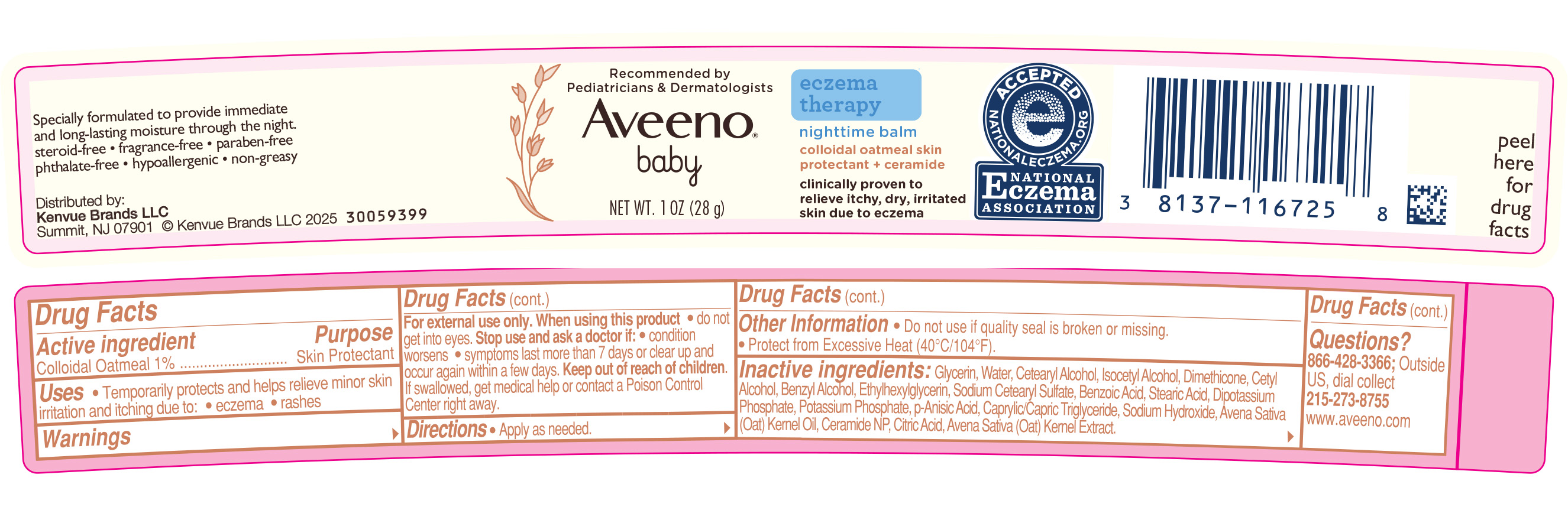 DRUG LABEL: Aveeno Baby Eczema Therapy Nighttime Balm
NDC: 69968-0540 | Form: CREAM
Manufacturer: Kenvue Brands LLC
Category: otc | Type: HUMAN OTC DRUG LABEL
Date: 20250304

ACTIVE INGREDIENTS: OATMEAL 10 mg/1 g
INACTIVE INGREDIENTS: GLYCERIN; WATER; CETOSTEARYL ALCOHOL; ISOCETYL ALCOHOL; DIMETHICONE; CETYL ALCOHOL; BENZYL ALCOHOL; ETHYLHEXYLGLYCERIN; SODIUM CETOSTEARYL SULFATE; BENZOIC ACID; STEARIC ACID; DIBASIC POTASSIUM PHOSPHATE; POTASSIUM PHOSPHATE, UNSPECIFIED FORM; P-ANISIC ACID; MEDIUM-CHAIN TRIGLYCERIDES; SODIUM HYDROXIDE; OAT KERNEL OIL; CERAMIDE NP; CITRIC ACID MONOHYDRATE; OAT

Aveeno® baby eczema therapy nighttime balm

Drug Facts

Active Ingredient

Colloidal Oatmeal 1%

Purpose

Skin Protectant

Uses

- Temporarily protects and helps relieve minor skin irritation and itching due to:
  - eczema
  - rashes

Warnings

For external use only.

When using this product

- do not get into eyes.

Stop use and ask a doctor if:

- condition worsens
- symptoms last more than 7 days or clear up and occur again within a few days.

Keep out of reach of children. If swallowed, get medical help or contact a Poison Control Center right away.

Directions

- Apply as needed.

Other Information

- Do not use if quality seal is broken or missing.
- Protect from Excessive Heat (40°C/104°F).

Inactive Ingredients

Glycerin, Water, Cetearyl Alcohol, Isocetyl Alcohol, Dimethicone, Cetyl Alcohol, Benzyl Alcohol, Ethylhexylglycerin, Sodium Cetearyl Sulfate, Benzoic Acid, Stearic Acid, Dipotassium Phosphate, Potassium Phosphate, p-Anisic Acid, Caprylic/Capric Triglyceride, Sodium Hydroxide, Avena Sativa (Oat) Kernel Oil, Ceramide NP, Citric Acid, Avena Sativa (Oat) Kernel Extract

Questions?

866-428-3366; Outside US, dial collect 215-273-8755 www.aveeno.com

Distributed by:
Kenvue Brands LLC
Summit, NJ 07901

PRINCIPAL DISPLAY PANEL - 28 g Jar Label

Recommended by

Pediatricians & Dermatologists

Aveeno®

baby

NET WT. 1 OZ (28 g)
eczema
therapy

nighttime balm

colloidal oatmeal skin
protectant + ceramide

clinically proven to

relieve itchy, dry, irritated

skin due to eczema

ACCEPTED
e
NATIONALECZEMA.ORG

NATIONAL
ECZEMA
ASSOCIATION